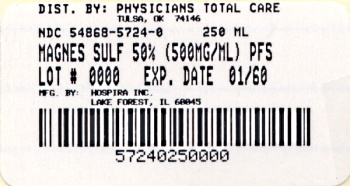 DRUG LABEL: Magnesium Sulfate
NDC: 54868-5724 | Form: INJECTION, SOLUTION
Manufacturer: Physicians Total Care, Inc.
Category: prescription | Type: HUMAN PRESCRIPTION DRUG LABEL
Date: 20100527

ACTIVE INGREDIENTS: MAGNESIUM SULFATE HEPTAHYDRATE 500 mg/1 mL
INACTIVE INGREDIENTS: Water; Sulfuric Acid; Sodium Hydroxide

MAGNESIUM SULFATE
INJECTION, USP

Ansyr™ Plastic Syringe

Rx only

DESCRIPTION

Magnesium Sulfate Injection, USP is a sterile solution of magnesium sulfate heptahydrate in Water for Injection, USP administered by the intravenous or intramuscular routes as an electrolyte replenisher or anticonvulsant. Must be diluted before I.V. use. May contain sulfuric acid and/or sodium hydroxide for pH adjustment. The pH is 6.0 (5.5 to 7.0). The 50% concentration has an osmolarity of 4.06 mOsmol/mL (calc.).

The solution contains no bacteriostat, antimicrobial agent or added buffer (except for pH adjustment) and is intended only for use as a single-dose injection. When smaller doses are required the unused portion should be discarded with the entire unit.

Magnesium Sulfate, USP heptahydrate is chemically designated MgSO4 • 7H2O with molecular weight of 246.48 and occurs as colorless crystals or white powder freely soluble in water.

The plastic syringe is molded from a specially formulated polypropylene. Water permeates from inside the container at an extremely slow rate which will have an insignificant effect on solution concentration over the expected shelf life. Solutions in contact with the plastic container may leach out certain chemical components from the plastic in very small amounts; however, biological testing was supportive of the safety of the syringe material.

CLINICAL PHARMACOLOGY

Magnesium (Mg^++) is an important cofactor for enzymatic reactions and plays an important role in neurochemical transmission and muscular excitability.

As a nutritional adjunct in hyperalimentation, the precise mechanism of action for magnesium is uncertain. Early symptoms of hypomagnesemia (less than 1.5 mEq/liter) may develop as early as three to four days or within weeks.

Predominant deficiency effects are neurological, e.g., muscle irritability, clonic twitching and tremors. Hypocalcemia and hypokalemia often follow low serum levels of magnesium. While there are large stores of magnesium present intracellularly and in the bones of adults, these stores often are not mobilized sufficiently to maintain plasma levels. Parenteral magnesium therapy repairs the plasma deficit and causes deficiency symptoms and signs to cease.

Magnesium prevents or controls convulsions by blocking neuromuscular transmission and decreasing the amount of acetylcholine liberated at the end plate by the motor nerve impulse. Magnesium is said to have a depressant effect on the central nervous system (CNS), but it does not adversely affect the mother, fetus or neonate when used as directed in eclampsia or pre-eclampsia. Normal plasma magnesium levels range from 1.5 to 2.5 mEq/liter.

As plasma magnesium rises above 4 mEq/liter, the deep tendon reflexes are first decreased and then disappear as the plasma level approaches 10 mEq/liter. At this level respiratory paralysis may occur. Heart block also may occur at this or lower plasma levels of magnesium. Serum magnesium concentrations in excess of 12 mEq/L may be fatal.

Magnesium acts peripherally to produce vasodilation. With low doses only flushing and sweating occur, but larger doses cause lowering of blood pressure. The central and peripheral effects of magnesium poisoning are antagonized to some extent by intravenous administration of calcium.

Pharmacokinetics

With intravenous administration the onset of anticonvulsant action is immediate and lasts about 30 minutes. Following intramuscular administration the onset of action occurs in about one hour and persists for three to four hours. Effective anticonvulsant serum levels range from 2.5 to 7.5 mEq/liter. Magnesium is excreted solely by the kidney at a rate proportional to the plasma concentration and glomerular filtration.

INDICATIONS AND USAGE

Magnesium Sulfate Injection, USP is suitable for replacement therapy in magnesium deficiency, especially in acute hypomagnesemia accompanied by signs of tetany similar to those observed in hypocalcemia. In such cases, the serum magnesium (Mg^++) level is usually below the lower limit of normal (1.5 to 2.5 mEq/liter) and the serum calcium (Ca^++) level is normal (4.3 to 5.3 mEq/liter) or elevated.

In total parenteral nutrition (TPN), magnesium sulfate may be added to the nutrient admixture to correct or prevent hypomagnesemia which can arise during the course of therapy.

Magnesium Sulfate Injection, USP is also indicated as a parenteral anticonvulsant for the prevention and control of seizures (convulsions) in severe toxemia of pregnancy. It effectively prevents and controls the convulsions of eclampsia without producing deleterious depression of the central nervous system of the mother or infant. However, other effective drugs are available for this purpose.

CONTRAINDICATIONS

Parenteral administration of the drug is contraindicated in patients with heart block or myocardial damage.

WARNINGS

Intravenous use in eclampsia should be reserved for immediate control of life-threatening convulsions.

Parenteral use in the presence of renal insufficiency may lead to magnesium intoxication.

Warning: This product contains aluminum that may be toxic. Aluminum may reach toxic levels with prolonged parenteral administration if kidney function is impaired. Premature neonates are particularly at risk because their kidneys are immature, and they require large amounts of calcium and phosphate solutions, which contain aluminum.

Research indicates that patients with impaired kidney function, including premature neonates, who receive parenteral levels of aluminum at greater than 4 to 5 mcg/kg/day accumulate aluminum at levels associated with central nervous system and bone toxicity. Tissue loading may occur even at lower rates of administration.

PRECAUTIONS

General

Administer with caution if flushing and sweating occurs. When barbiturates, narcotics or other hypnotics (or systemic anesthetics) are to be given in conjunction with magnesium, their dosage should be adjusted with caution because of additive CNS depressant effects of magnesium.

Because magnesium is removed from the body solely by the kidneys, the drug should be used with caution in patients with renal impairment. Urine output should be maintained at a level of 100 mL or more during the four hours preceding each dose. Monitoring serum magnesium levels and the patient’s clinical status is essential to avoid the consequences of overdosage in toxemia. Clinical indications of a safe dosage regimen include the presence of the patellar reflex (knee jerk) and absence of respiratory depression (approximately 16 breaths or more/minute). When repeated doses of the drug are given parenterally, knee jerk reflexes should be tested before each dose and if they are absent, no additional magnesium should be given until they return. Serum magnesium levels usually sufficient to control convulsions range from 3 to 6 mg/100 mL (2.5 to 5 mEq/liter). The strength of the deep tendon reflexes begins to diminish when magnesium levels exceed 4 mEq/liter. Reflexes may be absent at 10 mEq magnesium/liter, where respiratory paralysis is a potential hazard. An injectable calcium salt should be immediately available to counteract the potential hazards of magnesium intoxication in eclampsia.

50% Magnesium Sulfate Injection, USP must be diluted to a concentration of 20% or less prior to I.V. infusion. Rate of administration should be slow and cautious, to avoid producing hypermagnesemia. The 50% solution also should be diluted to 20% or less for intramuscular injection in infants and children.

Laboratory Tests

Magnesium sulfate injection should not be given unless hypomagnesemia has been confirmed and the serum concentration of magnesium is monitored. The normal serum level is 1.5 to 2.5 mEq/L.

Drug Interactions

CNS Depressants — When barbiturates, narcotics or other hypnotics (or systemic anesthetics), or other CNS depressants are to be given in conjunction with magnesium, their dosage should be adjusted with caution because of additive CNS depressant effects of magnesium. CNS depression and peripheral transmission defects produced by magnesium may be antagonized by calcium.

Neuromuscular Blocking Agents — Excessive neuromuscular block has occurred in patients receiving parenteral magnesium sulfate and a neuromuscular blocking agent; these drugs should be administered concomitantly with caution.

Cardiac Glycosides — Magnesium sulfate should be administered with extreme caution in digitalized patients, because serious changes in cardiac conduction which can result in heart block may occur if administration of calcium is required to treat magnesium toxicity.

Pregnancy Category A.

Studies in pregnant women have not shown that magnesium sulfate injection increases the risk of fetal abnormalities if administered during all trimesters of pregnancy. If this drug is used during pregnancy, the possibility of fetal harm appears remote. However, because studies cannot rule out the possibility of harm, magnesium sulfate injection should be used during pregnancy only if clearly needed.

When administered by continuous intravenous infusion (especially for more than 24 hours preceding delivery) to control convulsions in toxemic mothers, the newborn may show signs of magnesium toxicity, including neuromuscular or respiratory depression. See OVERDOSAGE.

Nursing Mothers

Since magnesium is distributed into milk during parenteral magnesium sulfate administration, the drug should be used with caution in nursing women.

Geriatrics

Geriatric patients often require reduced dosage because of impaired renal function. In patients with severe impairment, dosage should not exceed 20 g in 48 hours. Serum magnesium should be monitored in such patients.

ADVERSE REACTIONS

The adverse effects of parenterally administered magnesium usually are the result of magnesium intoxication. These include flushing, sweating, hypotension, depressed reflexes, flaccid paralysis, hypothermia, circulatory collapse, cardiac and central nervous system depression proceeding to respiratory paralysis. Hypocalcemia with signs of tetany secondary to magnesium sulfate therapy for eclampsia has been reported.

OVERDOSAGE

Magnesium intoxication is manifested by a sharp drop in blood pressure and respiratory paralysis. Disappearance of the patellar reflex is a useful clinical sign to detect the onset of magnesium intoxication. In the event of overdosage artificial ventilation must be provided until a calcium salt can be injected intravenously to antagonize the effects of magnesium.

For Treatment of Overdose

Artificial respiration is often required. Intravenous calcium, 10 to 20 mL of a 5% solution (diluted if desirable with isotonic sodium chloride for injection) is used to counteract effects of hypermagnesemia. Subcutaneous physostigmine, 0.5 to 1 mg may be helpful.

Hypermagnesemia in the newborn may require resuscitation and assisted ventilation via endotracheal intubation or intermittent positive pressure ventilation as well as intravenous calcium.

DOSAGE AND ADMINISTRATION

Dosage of magnesium sulfate must be carefully adjusted according to individual requirements and response, and administration of the drug should be discontinued as soon as the desired effect is obtained.

Both intravenous and intramuscular administration are appropriate. Intramuscular administration of the undiluted 50% solution results in therapeutic plasma levels in 60 minutes, whereas I.V. doses will provide a therapeutic level almost immediately. The rate of I.V. injection should generally not exceed 150 mg/minute (1.5 mL of a 10% concentration or its equivalent), except in severe eclampsia with seizures (see below).

Solutions for intravenous infusion must be diluted to a concentration of 20% or less prior to administration. The diluents commonly used are 5% Dextrose Injection, USP and 0.9% Sodium Chloride Injection, USP. Deep intramuscular injection of the undiluted (50%) solution is appropriate for adults, but the solution should be diluted to a 20% or less concentration prior to such injection in children.

In Magnesium Deficiency

In the treatment of mild magnesium deficiency, the usual adult dose is 1 g, equivalent to 8.12 mEq of magnesium (2 mL of the 50% solution) injected intramuscularly every six hours for four doses (equivalent to a total of 32.5 mEq of magnesium per 24 hours). For severe hypomagnesemia, as much as 250 mg (approximately 2 mEq) per kg of body weight (0.5 mL of the 50% solution) may be given intramuscularly within a period of four hours if necessary. Alternatively, 5 g, (approximately 40 mEq) can be added to one liter of 5% Dextrose Injection, USP or 0.9% Sodium Chloride Injection, USP for slow intravenous infusion over a three-hour period. In the treatment of deficiency states, caution must be observed to prevent exceeding the renal excretory capacity.

In Hyperalimentation

In total parenteral nutrition, maintenance requirements for magnesium are not precisely known. The maintenance dose used in adults ranges from 8 to 24 mEq (1 to 3 g) daily; for infants, the range is 2 to 10 mEq (0.25 to 1.25 g) daily.

In Eclampsia

In severe pre-eclampsia or eclampsia, the total initial dose is 10 to 14 g of magnesium sulfate. Intravenously, a dose of 4 to 5 g in 250 mL of 5% Dextrose Injection, USP or 0.9% Sodium Chloride Injection, USP may be infused. Simultaneously, intramuscular doses of up to 10 g (5 g or 10 mL of the undiluted 50% solution in each buttock) are given. Alternatively, the initial intravenous dose of 4 g may be given by diluting the 50% solution to a 10 or 20% concentration; the diluted fluid (40 mL of a 10% solution or 20 mL of a 20% solution) may then be injected intravenously over a period of three to four minutes. Subsequently, 4 to 5 g (8 to 10 mL of the 50% solution) are injected intramuscularly into alternate buttocks every four hours, depending on the continuing presence of the patellar reflex and adequate respiratory function. Alternatively, after the initial I.V. dose, some clinicians administer 1 to 2 g/hour by constant I.V. infusion. Therapy should continue until paroxysms cease. A serum magnesium level of 6 mg/100 mL is considered optimal for control of seizures. A total daily (24 hr) dose of 30 to 40 g should not be exceeded. In the presence of severe renal insufficiency, the maximum dosage of magnesium sulfate is 20 grams/48 hours and frequent serum magnesium concentrations must be obtained.

Other Uses

In counteracting the muscle-stimulating effects of barium poisoning, the usual dose of magnesium sulfate is 1 to 2 g given I.V.

For controlling seizures associated with epilepsy, glomerulonephritis or hypothyroidism, the usual adult dose is 1 g administered I.M. or I.V.

In paroxysmal atrial tachycardia, magnesium should be used only if simpler measures have failed and there is no evidence of myocardial damage. The usual dose is 3 to 4 g (30 to 40 mL of a 10% solution) administered I.V. over 30 seconds with extreme caution.

For reduction of cerebral edema, 2.5 g (25 mL of a 10% solution) is given I.V.

Incompatibilities

Magnesium sulfate in solution may result in a precipitate formation when mixed with solutions containing:

Alcohol (in high | Heavy Metals
concentrations) | Hydrocortisone sodium
Alkali carbonates and | succinate
bicarbonates | Phosphates
Alkali hydroxides | Polymixin B sulfate
Arsenates | Procaine hydrochloride
Barium | Salicylates
Calcium | Strontium
Clindamycin phosphate | Tartrates

The potential incompatibility will often be influenced by the changes in the concentration of reactants and the pH of the solutions.

It has been reported that magnesium may reduce the antibiotic activity of streptomycin, tetracycline and tobramycin when given together.

Parenteral drug products should be inspected visually for particulate matter and discoloration prior to administration, whenever solution and container permit.

HOW SUPPLIED

Magnesium Sulfate Injection, USP is supplied in single-dose containers as follows:

NDC No. | Container | Total; Amount | Concentration | mEq; Mg^++/mL
54868-5724-0; 25 x 10 mL Vials | Ansyr™; Plastic Syringe | 5 g/10 mL | 50% | 4 mEq/mL

Do not administer unless solution is clear and container is undamaged. Discard unused portion.

Store at 20 to 25°C (68 to 77°F). [See USP Controlled Room Temperature.]

Revised: November, 2009

Printed in USA | EN-2303

Hospira, Inc., Lake Forest, IL 60045 USA

Additional barcode labeling by:
Physicians Total Care, Inc.
Tulsa, OK 74146

PRINCIPAL DISPLAY PANEL

Magnesium Sulfate Injection, USP

NDC 54868-5724-0

500 mg/mL